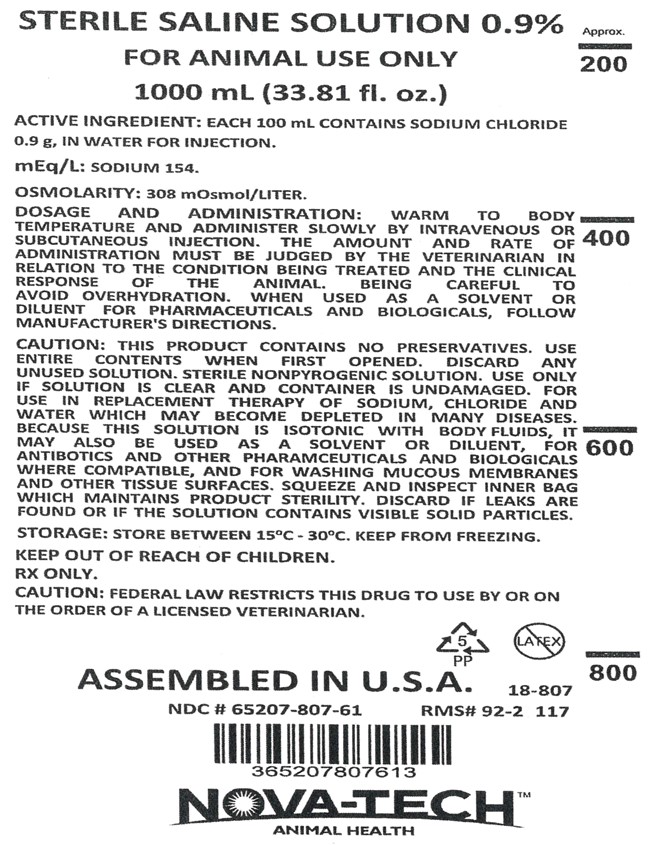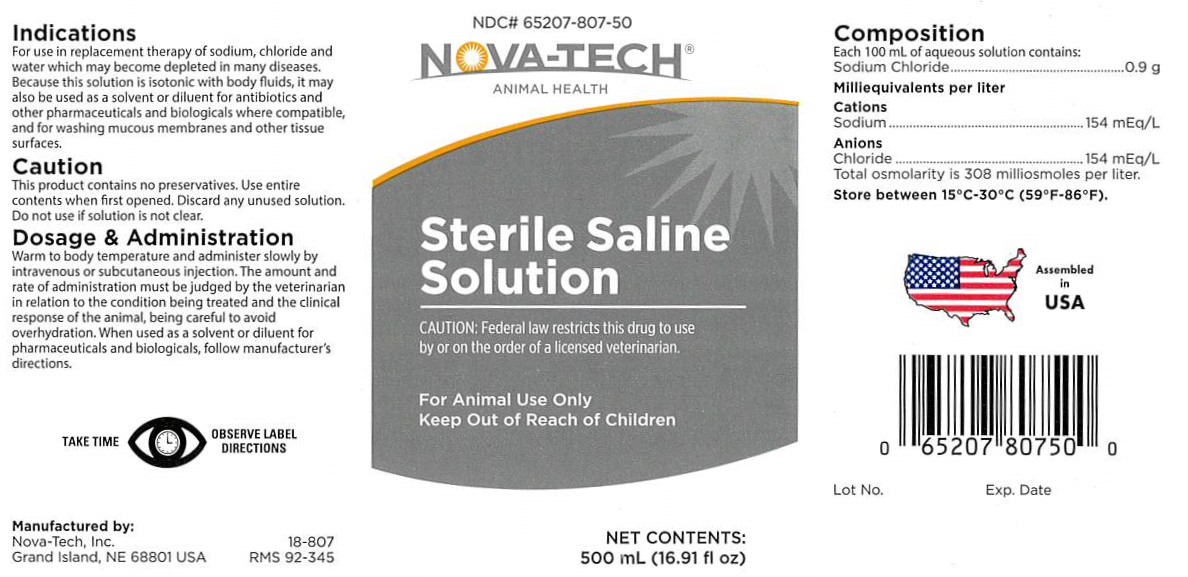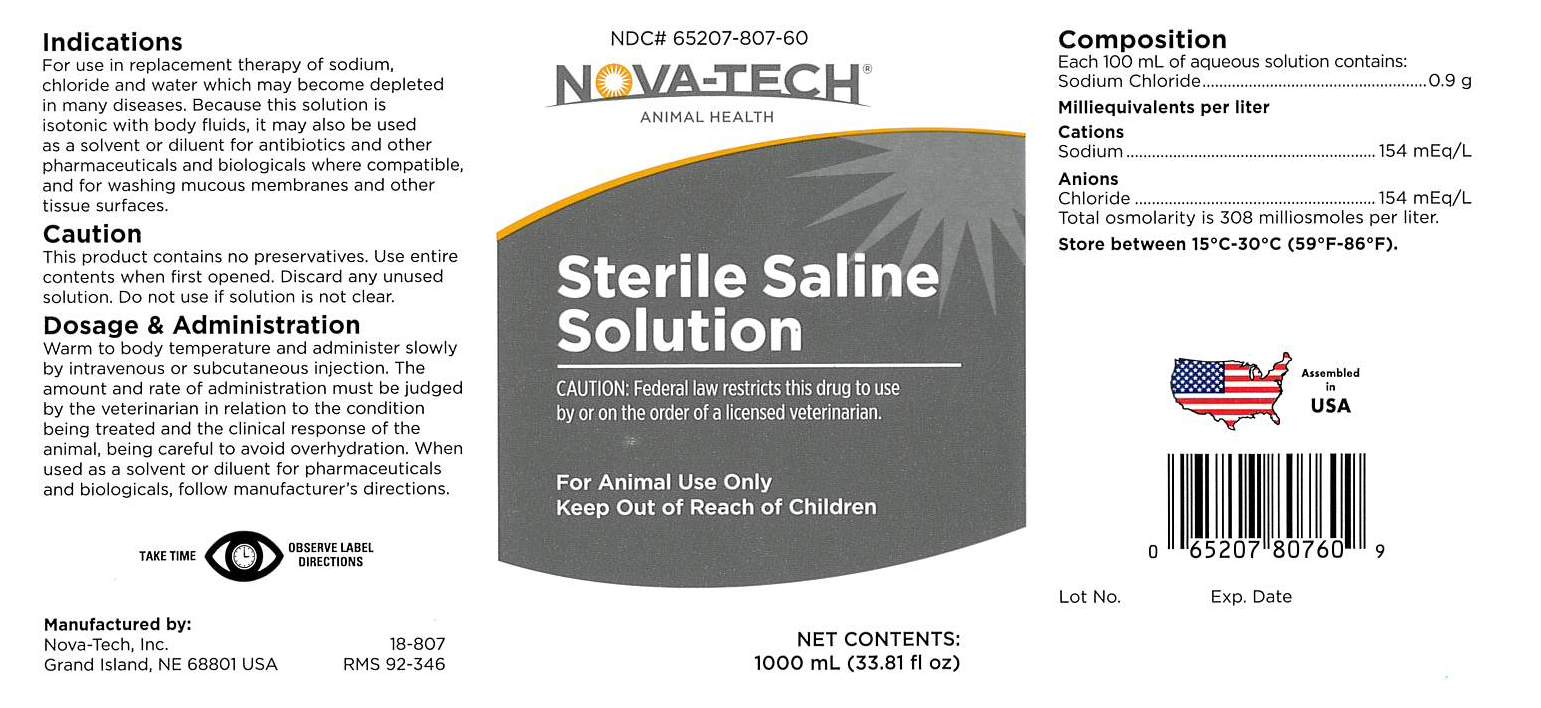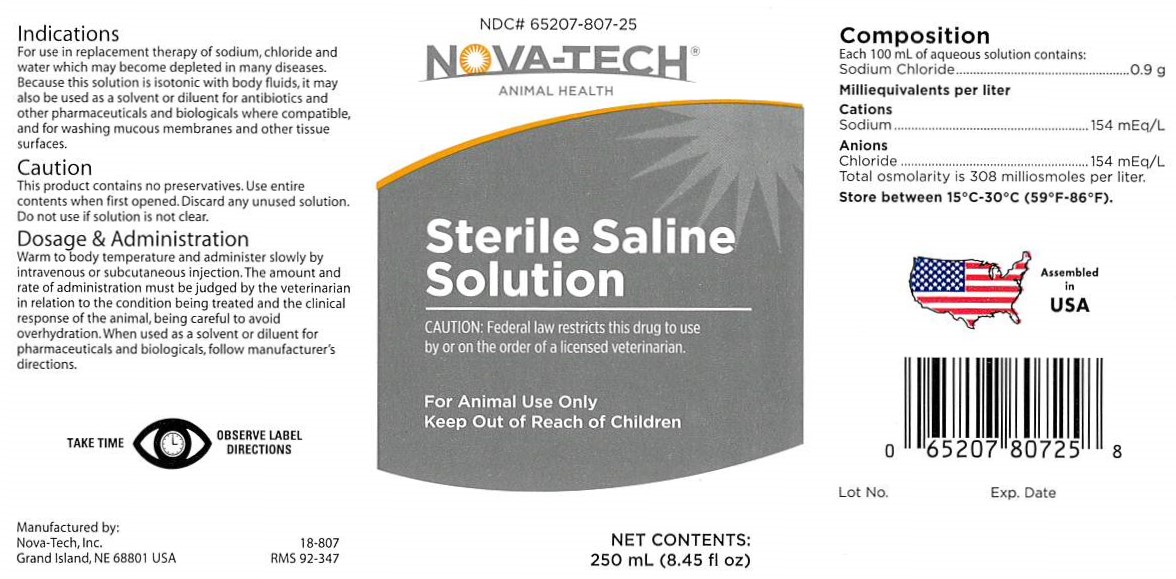 DRUG LABEL: Sterile Saline Solution
NDC: 65207-807 | Form: INJECTION, SOLUTION
Manufacturer: Nova-Tech, Inc.
Category: animal | Type: PRESCRIPTION ANIMAL DRUG LABEL
Date: 20240104

ACTIVE INGREDIENTS: Sodium Chloride 0.9 g/100 mL

Sterile Saline Solution

INDICATIONS

For use in replacement therapy of sodium, chloride and water which may become depleted in many diseases. Because this solution is isotonic with body fluids, it may also be used as a solvent or diluent for antibiotics and other pharmaceuticals and biologicals where compatible, and for washing mucous membranes and other tissue surfaces.

CAUTION

This product contains no preservatives. Use entire contents when first opened. Discard any unused solution. Do not use if solution is not clear.

terile nonpyrogenic solution. Use only if solution is clear and container is undamaged. For use in replacement therapy of Sodium, Chloride and Water which may become depleted in many diseases. Because this solution is isotonic with body fluids, it may also be used as a solvent or diluent, for antibiotics and other pharamceuticals and biologicals where compatible, and for washing mucous membranes and other tissue surfaces. Squeeze and inspect inner bag which maintains product sterility. Discard if leaks are found or if the solution contains visible solid particles.

DOSAGE AND ADMINISTRATION

Warm to body temperature and administer slowly by intravenous or subcutaneous injection. The amount and rate of administration must be judged by the veterinarian in relation to the condition being treated and the clinical response of the animal, being careful to avoid overhydration. When used as a solvent or diluent for pharmaceuticals and biologicals, follow manufacturer's directions.

VETERINARY INDICATIONS

FOR ANIMAL USE ONLY

KEEP OUT OF REACH OF CHILDREN

RX Only

CAUTION:

Federal law restricts this drug to use by or on the order of a licensed veterinarian.

COMPOSITION

Each 100 mL of aqueous solution contains:

Sodium Chloride ....................................... 0.9 g

Milliequivalents per liter

Cations

Sodium ....................................... 154 mEq/L

Anions

Chloride ..................................... 154 mEq/L

Total osmolarity is 308 milliosmoles per liter.

STORAGE AND HANDLING

Store between 15°C and 30°C (59°F and 86°F). Keep from freezing.

PRECAUTIONS

TAKE TIME OBSERVE LABEL DIRECTIONS

INFORMATION FOR OWNERS/CAREGIVERS

Manufactured by:

Nova-Tech, Inc.

Grand Island, NE 68801 USA

18-807

RMS# 92-346

NDC: 65207-807-60

Net Contents

1000 mL (33.81 fl oz)

Assembled in USA

Lot No.

Exp. Date

RMS# 92-2117

NDC: 65207-807-61

365207807613